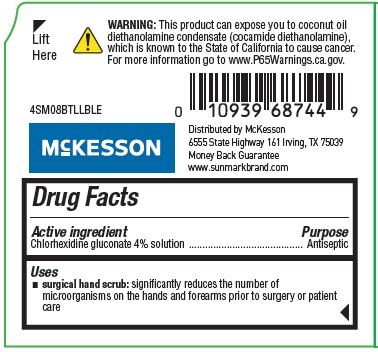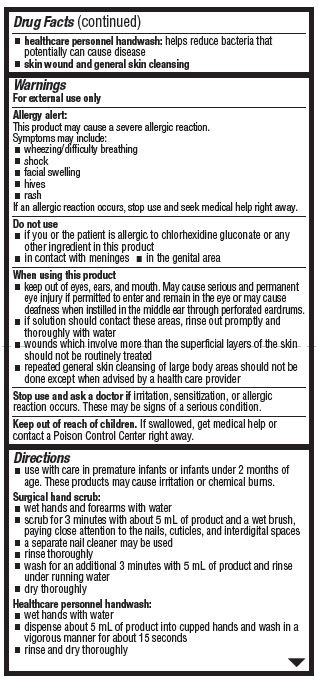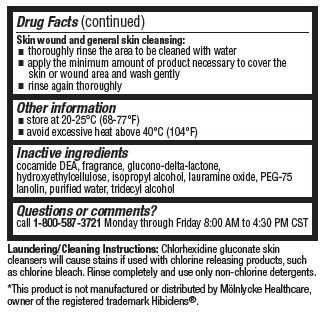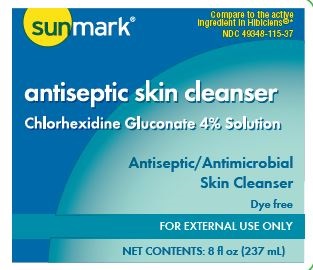 DRUG LABEL: Antiseptic Skin Cleanser
NDC: 49348-115 | Form: LIQUID
Manufacturer: Strategic Sourcing Services, LLC
Category: otc | Type: HUMAN OTC DRUG LABEL
Date: 20201028

ACTIVE INGREDIENTS: CHLORHEXIDINE GLUCONATE 4 mg/100 mL
INACTIVE INGREDIENTS: COCO DIETHANOLAMIDE; PEG-75 LANOLIN; HYDROXYETHYL CELLULOSE (2000 CPS AT 1%); ISOPROPYL ALCOHOL; WATER; TRIDECYL ALCOHOL; GLUCONOLACTONE

SunMart 8-oz

Active Ingredients

Chlorhexidine Gluconate 4% Solution

Purpose

Antiseptic

Uses

surgical hand scrub: significantly reduces the number of microorganisms on the hands and forearms prior to surgery or patient care

healthcare personnel handwash: helps reduce bacteria that potentially can cause disease

skin wound and general skin cleansing

Warnings

For external use only

Allergy alert:

This product may cause a severe allergic reaction.

Symptoms may include:

- wheezing/difficulty breathing
- shock
- facial swelling
- hives
- rash

If an allergic reaction occurs, stop use and seek medical help right away

Do not use

- if you are allergic to chlorhexidine gluconate or any other ingredient
- in contact with meninges
- in genital area

Keep out of reach of children.

If swallowed, get medical help or contact a Poison Control center right away

Stop use and ask doctor if

irritation, sensitization, or allergic reaction occurs. These may be signs of a serious condition.

When using this product

- keep out of eyes, ears, and mouth. May cause serious and permanent eye injuryif permitted to enter and remain in the eye or may cause deafness when instilled in the middle ear through perforated eardrums.
- if solution should contact these areas, rinse out promptly and thoroughly with water
- wounds which involve more than the superficial layers of the skin should not be routinely treated
- repeated general skin cleansing of large body areas should not be done except when advised by a health care provider

Directions

use with care in premature infants or infants under 2 months of age. These products may cause irritation or chemical burns.

Surgical hand scrub:

- wet hands and forearms under running water
- scrub for 3 minutes with about 5 mL of product and a wet brush, paying close attention to the nails, cuticles, and interdigital spaces
- a separate nail cleaner may be used
- rinse thoroughly
  - wash for an additional 3 minutes with 5 mL of product and rinse under running water
  - dry thoroughly

Healthcare personnel handwash:

- wet hands with water
- dispense about 5ml of product into cupped hands and wahs in vigorous manner for about 15 seconds
- rinse and dry thoroughly

Skin wound and normal skin cleansing:

- thoroughly rinse the area to be cleaned with water
- apply the minimum amount of product necessary to cover the skin or wound area and wash gently
- rinse again thoroughly

Other information

- store at 20°-25° C (68°-77° F)
- avoid excessive heat above 40° C (104° F)

Inactive ingredients

cocamide DEA, fragrance, glucono-delta-lactone, isopropyl alcohol, lauramine oxide, PEG-75 lanolin, purified water, tridecyl alcohol.

Questions of comments?

call 1-800-587-3721 Monday through Friday 8 AM to 4:30 PM CST

OTHER SAFETY INFORMATION

Warning: This product can expose you to coconut oil diethanolamine condensate (cocamide diethanolamine), which is known to the State of California to cause cancer.

Laundering/Cleaning Instructions: Chlorhexidine gluconate skin cleansers will cause stains if used with chlorine releasing products. Rinse completely and use non-chlorine detergents.

*This product is not manufactured or distributed by Mölnlycke Healthcare, owner of the registered trademark Hibiclens®.

PACKAGE LABEL

sunmark

Compare to the active ingredient in Hibiclens®

NDC 49348-115-37

antiseptic skin cleanser

Chlorhexidine Gluconate 4% Solution

Antiseptic/Antimicrobial

Skin Cleanser

Dye free

FOR EXTERNAL USE ONLY

NET CONTENTS: 8 fl oz (237 mL)